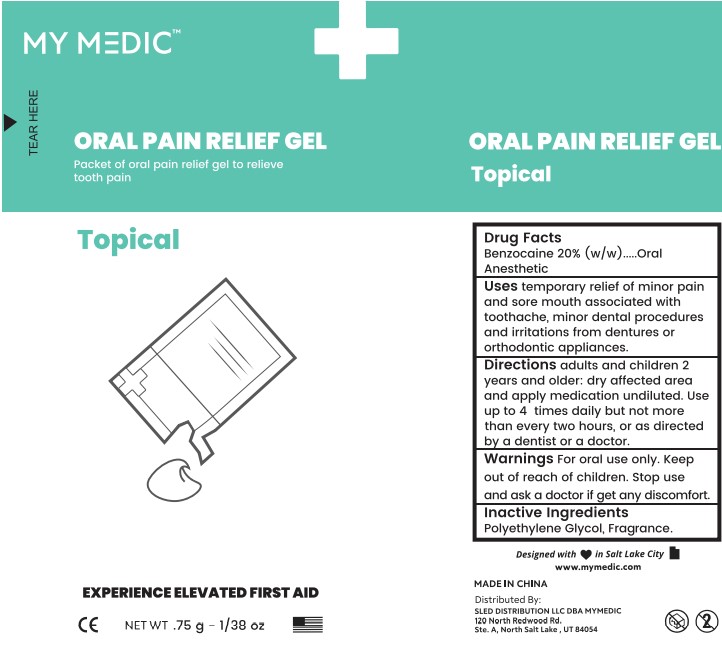 DRUG LABEL: Oral Pain Relief Gel
NDC: 81417-121 | Form: GEL
Manufacturer: Sled Distribution, LLC
Category: otc | Type: HUMAN OTC DRUG LABEL
Date: 20220325

ACTIVE INGREDIENTS: BENZOCAINE 200 mg/1 g
INACTIVE INGREDIENTS: POLYETHYLENE GLYCOL, UNSPECIFIED

Oral Pain Relief Gel

Drug Facts

Active ingredient

Benzocaine 20% (w/w)

Purpose

Oral anesthetic

Uses

For the temporary relief of minor pain and sore mouth associated with toothache, minor dental procedures and irritations from dentures or orthodontic appliances.

Warnings

For oral use only.

stop use and ask a doctor if get any discomfort.

Stop use and ask a dentist or doctor if

- sore mouth does not improve in 7 days
- irritation, pain, or redness persists or worsens
- swelling, rash, fever or other allergic reaction develops

Keep out of reach of children.

If accidentally swallowed get medical help or contact a Poison Control Center right away.

Directions

Adults and children (2 years and older):

Dry affected area and apply medication undiluted. Use up to 4 times daily, but not more than every two hours, or as directed by a dentist or doctor.

Inactive ingredients

Polyethylene Glycol, Fragrance

PACKAGE LABEL

Benzocaine 20% | Oral Anesthetic

NET WT 0.75 g